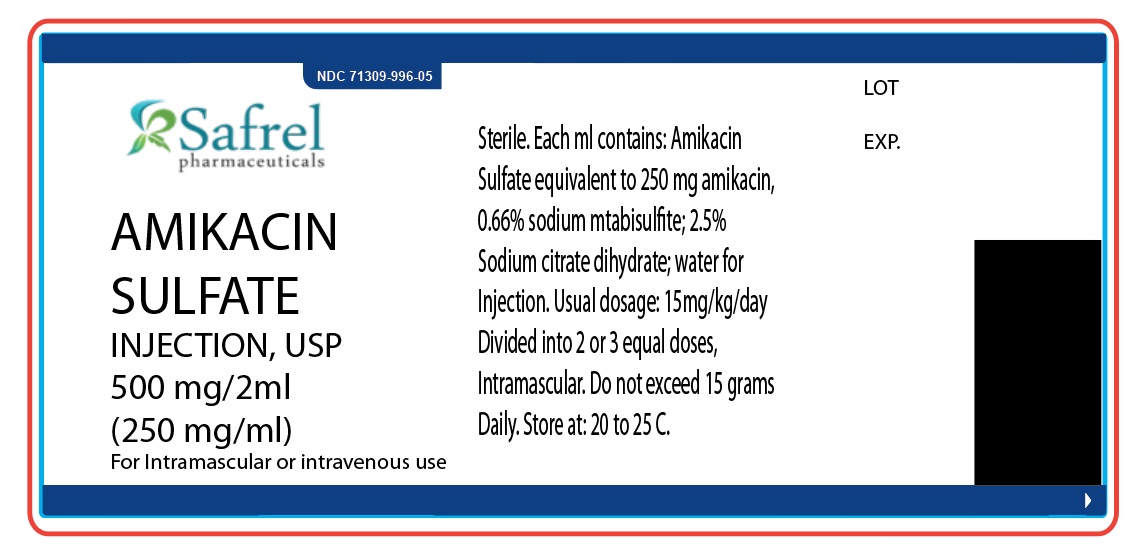 DRUG LABEL: Amikacin Sulfate Injection, 500 mg/2ml
NDC: 71309-996 | Form: INJECTION
Manufacturer: Safrel Pharmaceuticals, LLC.
Category: prescription | Type: HUMAN PRESCRIPTION DRUG LABEL
Date: 20210103

ACTIVE INGREDIENTS: AMIKACIN SULFATE 500 mg/1 1
INACTIVE INGREDIENTS: SULFURIC ACID; SODIUM METABISULFITE; SODIUM CITRATE

Amikacin Sulfate Injection, 500 mg / 2ml